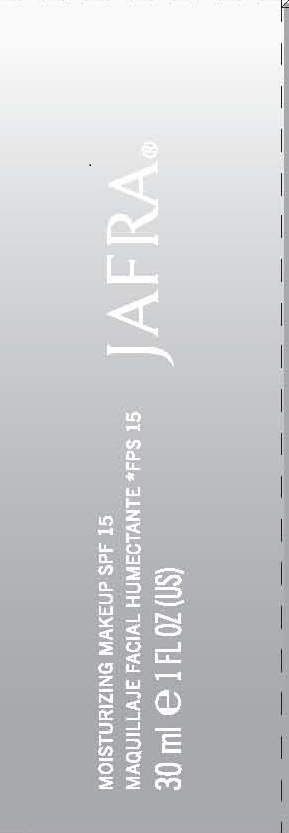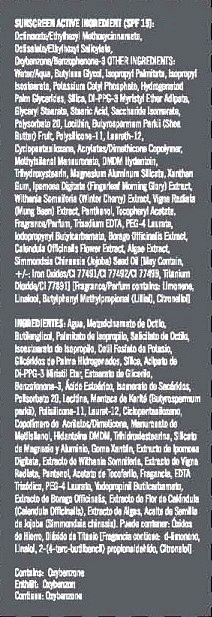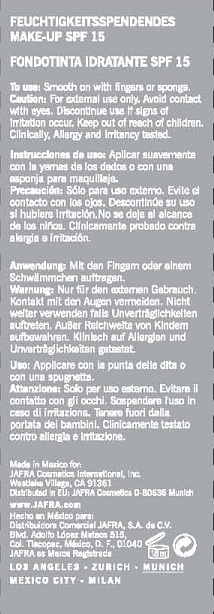 DRUG LABEL: MOISTURIZING MAKEUP
NDC: 68828-048 | Form: LOTION
Manufacturer: JAFRA COSMETICS INTERNATIONAL
Category: otc | Type: HUMAN OTC DRUG LABEL
Date: 20120501

ACTIVE INGREDIENTS: OCTINOXATE 6 g/100 mL; OCTISALATE 3 g/100 mL; OXYBENZONE 2 g/100 mL
INACTIVE INGREDIENTS: WATER; BUTYLENE GLYCOL; ISOPROPYL PALMITATE; ISOPROPYL ISOSTEARATE; POTASSIUM CETYL PHOSPHATE; HYDROGENATED PALM GLYCERIDES; GLYCERYL MONOSTEARATE; DI-PPG-3 MYRISTYL ETHER ADIPATE; SILICON DIOXIDE; STEARIC ACID; POLYSORBATE 20; LECITHIN, SOYBEAN; POLYSILICONE-15; LAURETH-12; CYCLOMETHICONE 5; CARBOMER INTERPOLYMER TYPE A (55000 MPA.S); DMDM HYDANTOIN; TRIHYDROXYSTEARIN; MAGNESIUM ALUMINUM SILICATE; XANTHAN GUM; PANTHENOL; IPOMOEA MAURITIANA TUBER; WITHANIA SOMNIFERA FLOWER; MUNG BEAN; ALPHA-TOCOPHEROL ACETATE; BORAGE; CALENDULA OFFICINALIS FLOWER; MACROCYSTIS PYRIFERA; JOJOBA OIL; EDETATE SODIUM; PEG-4 LAURATE; IODOPROPYNYL BUTYLCARBAMATE; FERRIC OXIDE RED; FERRIC OXIDE YELLOW; FERROSOFERRIC OXIDE; TITANIUM DIOXIDE; SACCHARIDE ISOMERATE; SHEA BUTTER; METHYLSILANOL ACETYLMETHIONATE

MOISTURIZING MAKEUP SPF-15

SUNSCREEN ACTIVE INGREDIENT (SPF 15):
OCTINOXATE/ETHYLHEXYL METHOXYCINNAMATE, OCTISALATE/ETHYLHEXYL SALICYLATE, OXYBENZONE/BENZOPHENONE-3

PURPOSE: SUNSCREEN

INACTIVE INGREDIENT

OTHER INGREDIENTS: WATER/AQUA, BUTYLENE GLYCOL, ISOPROPYL PALMITATE, ISOPROPYL ISOSTEARATE, POTASSIUM CETHYL PHOSPHATE, HYDROGENATED PALM GLYCERIDES, SILICA, DI-PPG-3 MYRISTYL ETHER ADIPATE, GLYCERYL STEARATE, STEARIC ACID, SACCHARIDE ISOMERATE, POLYSORBATE 20, LECITHIN, BUTYROSPERMUM PARKII (SHEA BUTTER) FRUIT, POLYSILICONE-11, LAURETH-12, CYCLOPENTASILOXANE, ACRYLATES/DIMETHICONE COPOLYMER, METHYLSILANOL MANNURONATE, DMDM HYDANTOIN, TRIHYDROXYSTEARIN, MAGNESIUM ALUMINUM SILICATE, XANTHAN GUM, IPOMOEA DIGITATA (FINGERLEAF MORNING GLORY) EXTRACT, WITHANIA SOMNIFERIA (WINTER CHERRY) EXTRACT, VIGNA RADIATA (MUNG BEAN) EXTRACT, PANTHENOL, TOCOPHERYL ACETATE, FRAGRANCE/PARFUM, TETRASODIUM EDTA, PEG-4 LAURATE, IODOPROPYNYL BUTYLCARBAMATE, BORAGO OFFICINALIS EXTRACT, CALENDULA OFFICINALIS FLOWER EXTRACT, ALGAE EXTRACT, SIMMONDSIA CHINENSIS (JOJOBA) SEED OIL [MAY CONTAIN, +/-: IRON OXIDES/CI 77491/CI 77492/CI 77499, TITANIUM DIOXIDE/CI 77891] [FRAGRANCE/PARFUM CONTAINS: LIMONENE, LINALOOL, BUTYLPHENYL METHYLPROPIONAL (LILIAL), CITRONELLOL]

INDICATIONS AND USAGE

MOISTURIZING MAKEUP WITH SPF 15

TO USE: SMOOTH ON WITH FINGERS OR SPONGE.

WARNINGS

DISCONTINUE USE IF SIGNS OF IRRITATION OCCUR.

KEEP OUT OF REACH OF CHILDREN.

OTHER SAFETY INFORMATION

CLINICALLY, ALLERGY AND IRRITANCY TESTED.

PACKAGE LABEL

JAFRA

MOISTURIZING MAKEUP SPF 15

30 ML / 1 FL OZ